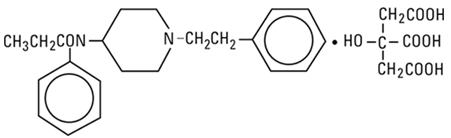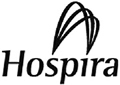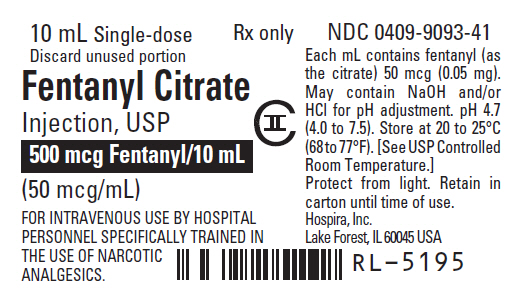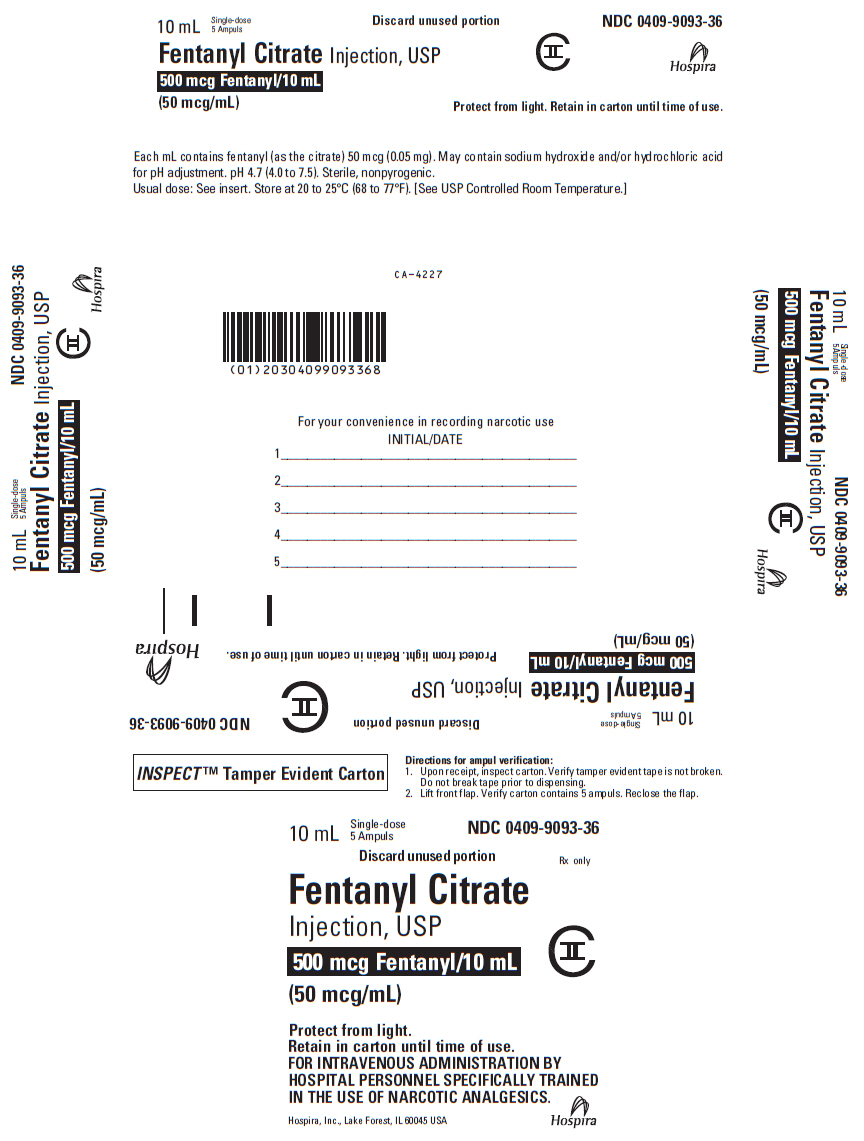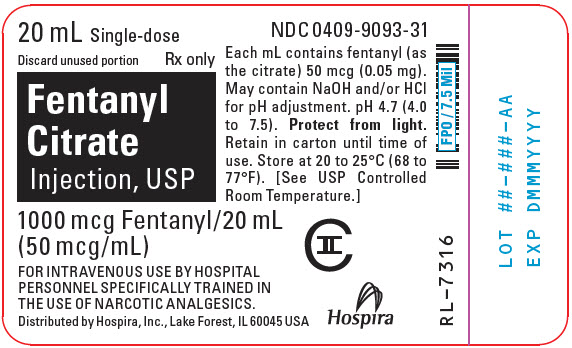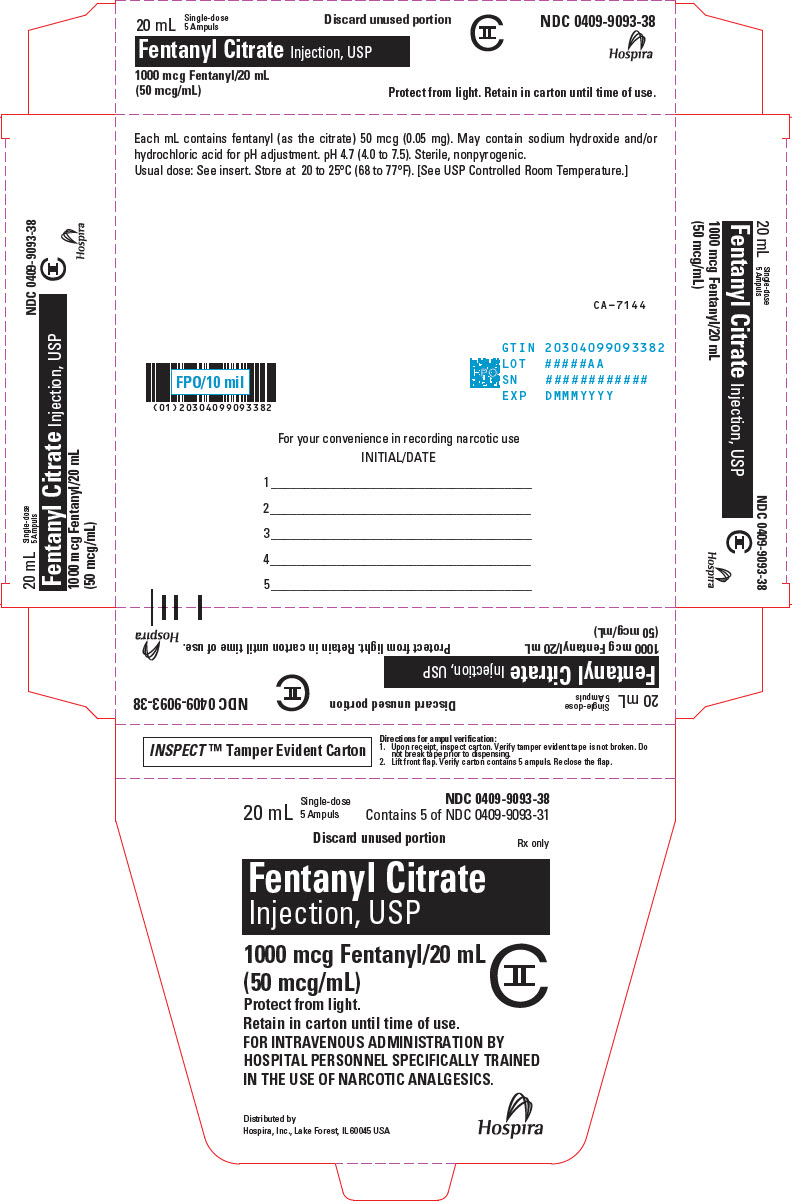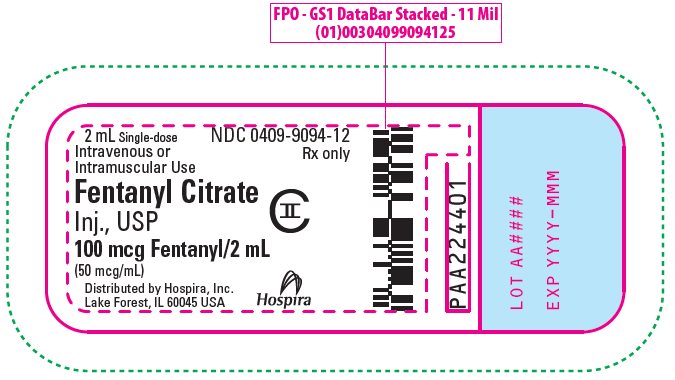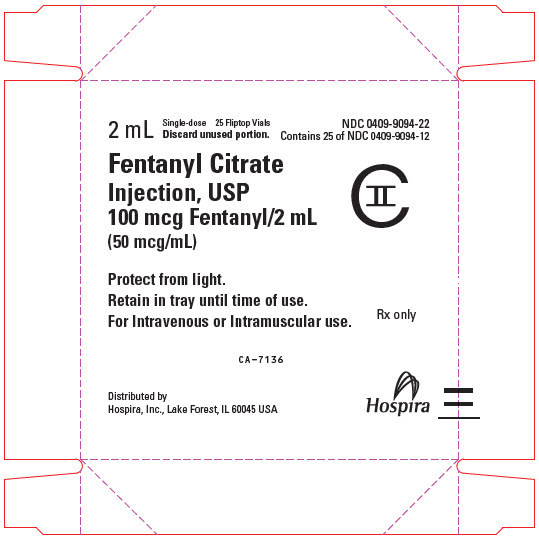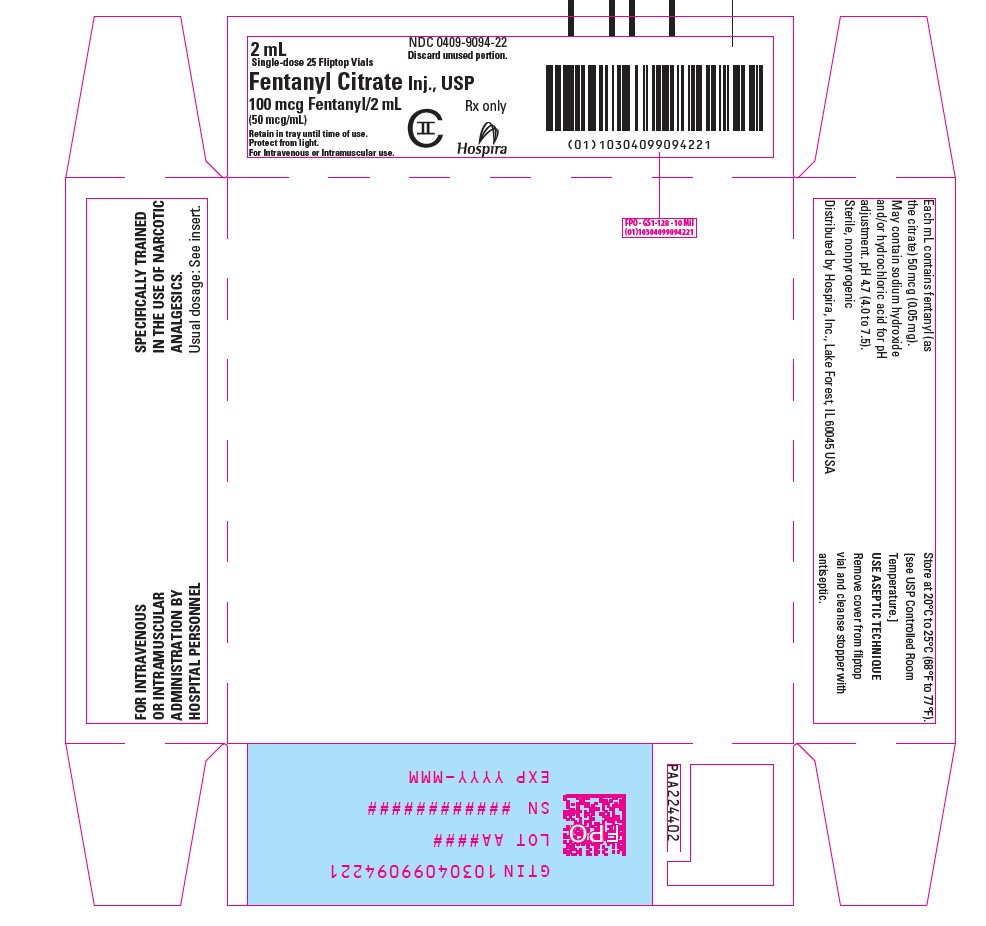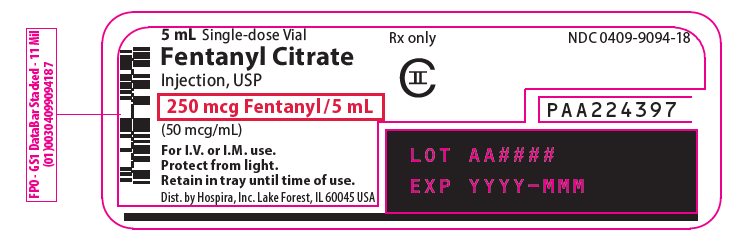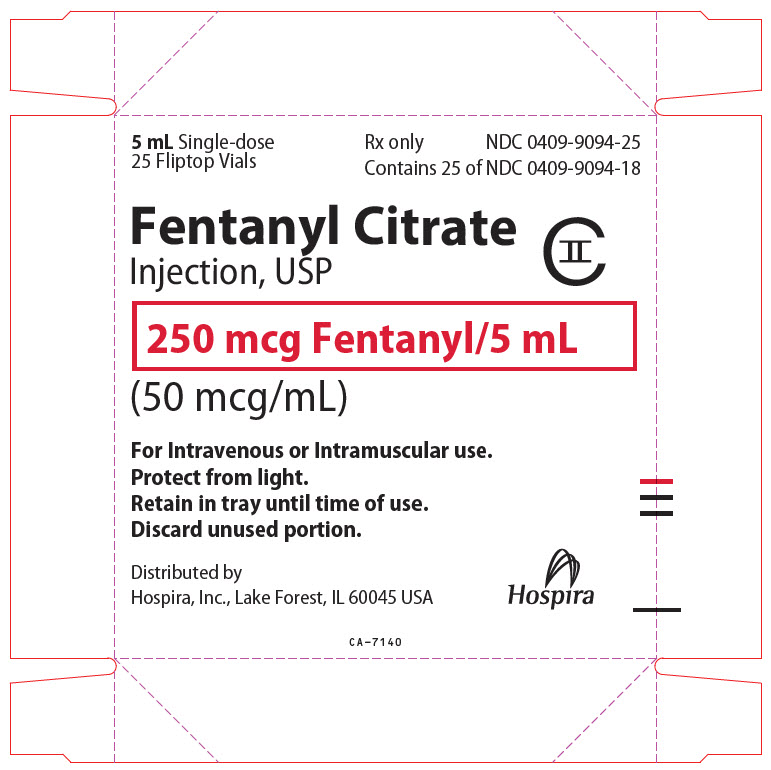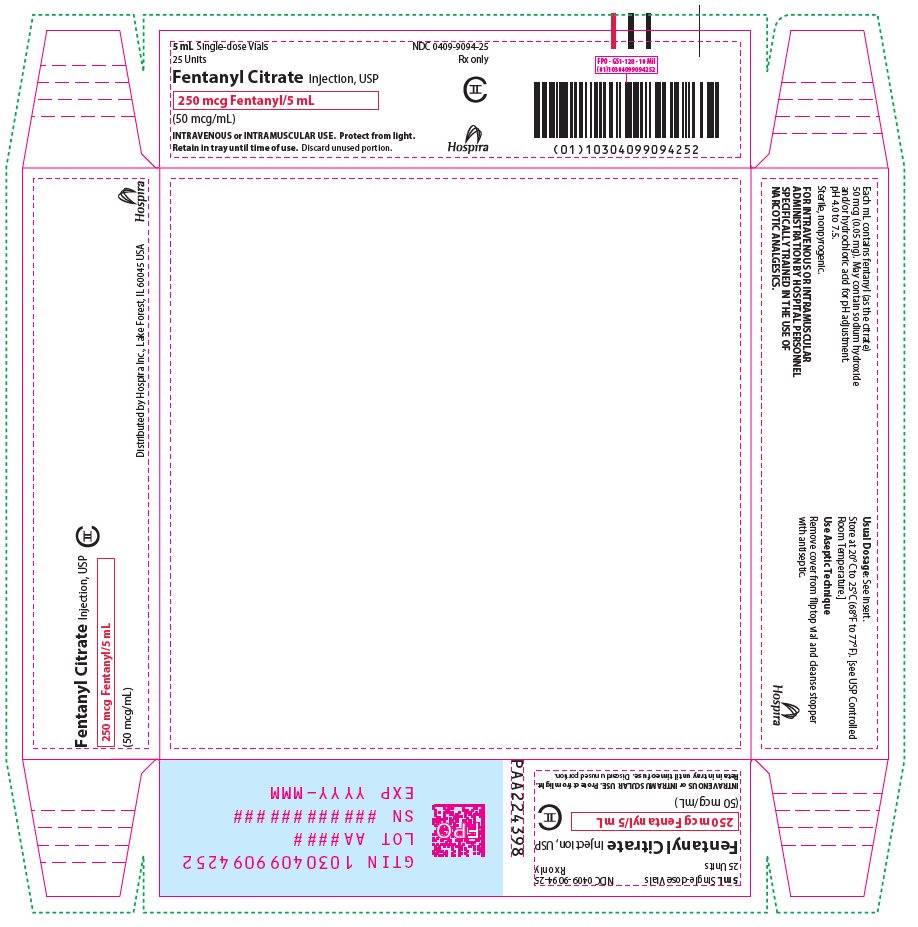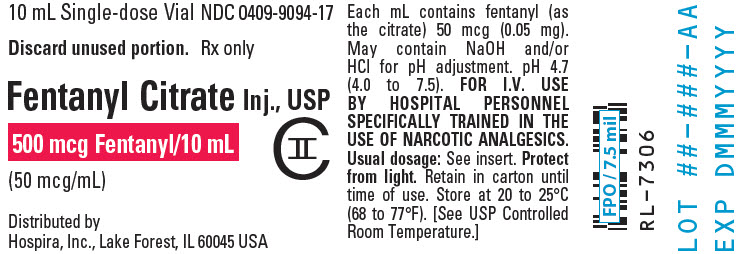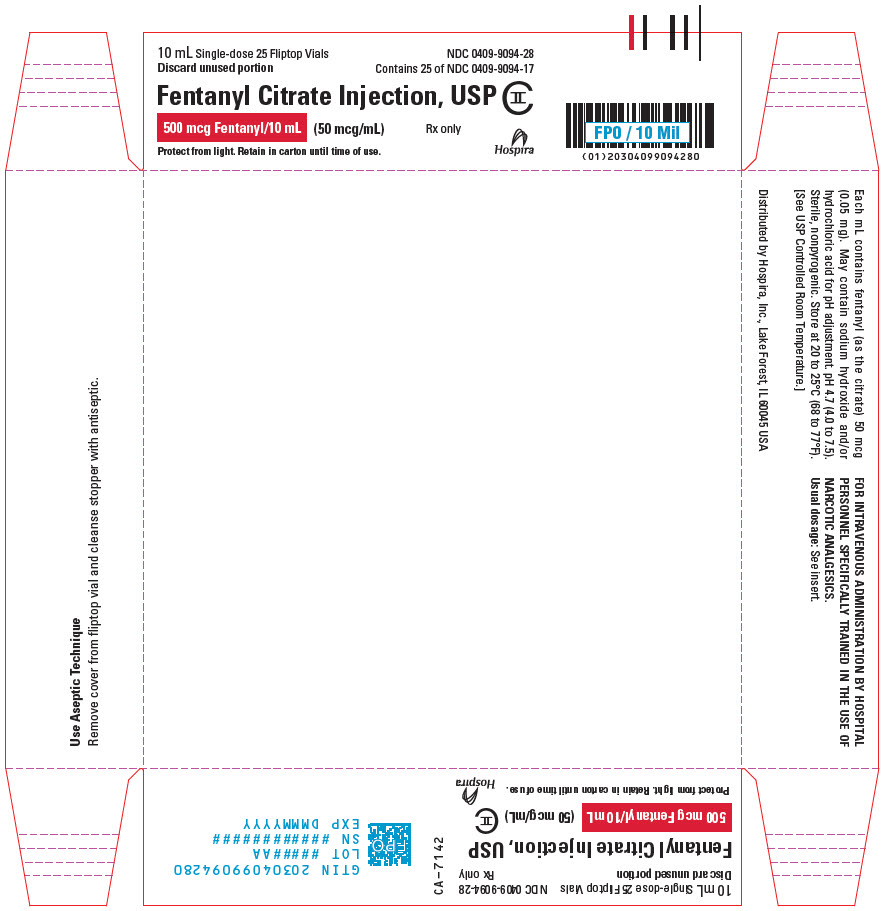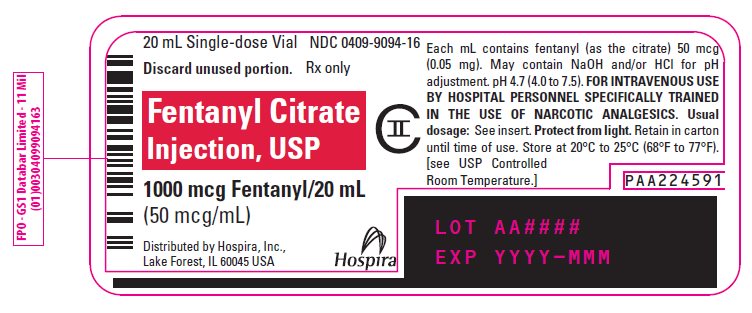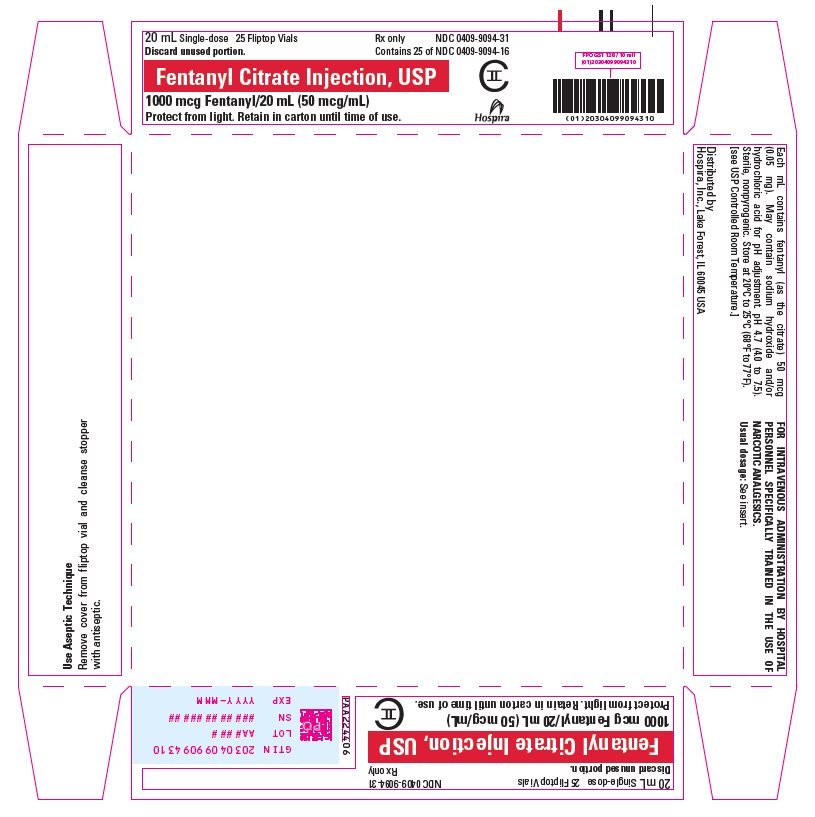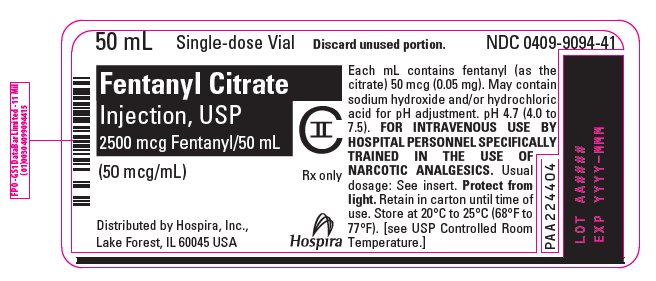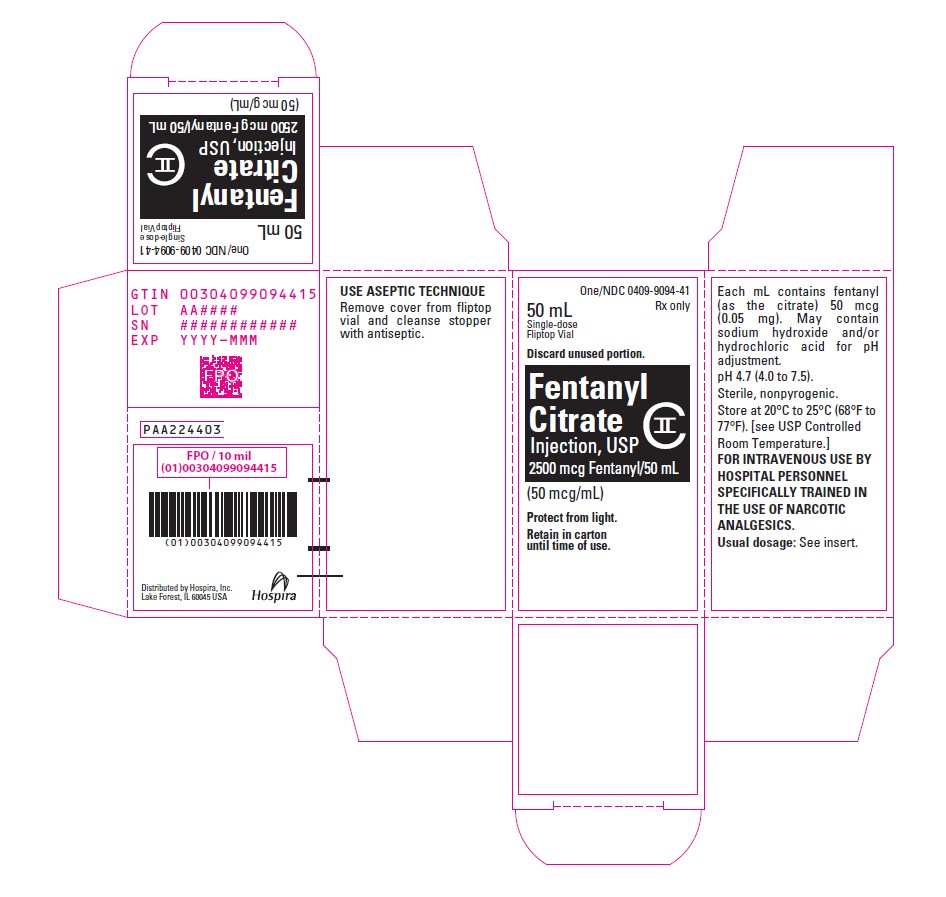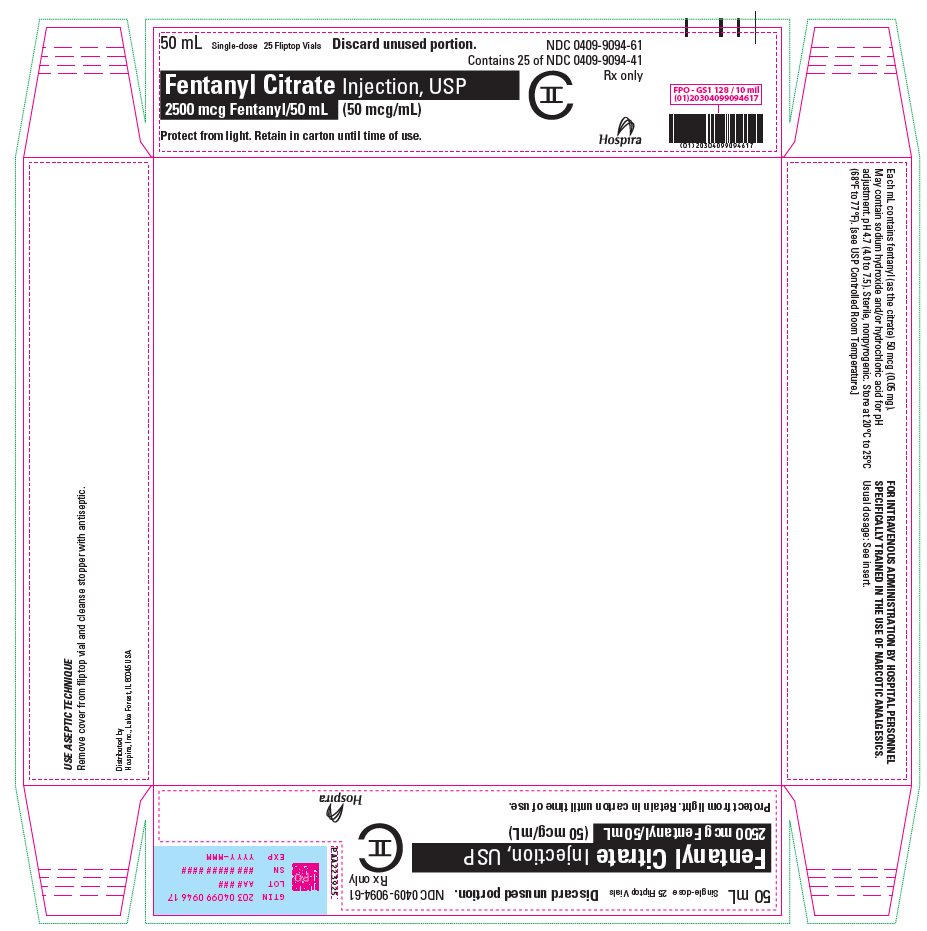 DRUG LABEL: Fentanyl Citrate
NDC: 0409-9093 | Form: INJECTION, SOLUTION
Manufacturer: Hospira, Inc.
Category: prescription | Type: HUMAN PRESCRIPTION DRUG LABEL
Date: 20260225
DEA Schedule: CII

ACTIVE INGREDIENTS: FENTANYL CITRATE 50 ug/1 mL
INACTIVE INGREDIENTS: SODIUM HYDROXIDE; HYDROCHLORIC ACID; WATER

HIGHLIGHTS OF PRESCRIBING INFORMATION

These highlights do not include all the information needed to use FENTANYL CITRATE INJECTION safely and effectively. See full prescribing information for FENTANYL CITRATE INJECTION.
FENTANYL CITRATE Injection, for Intravenous or Intramuscular use, CII
Initial U.S. Approval: 1968

RECENT MAJOR CHANGES

Dosage and Administration (2.1) | 12/2025
Warnings and Precautions (5.2, 5.3, 5.11) | 12/2025

WARNING: SERIOUS AND LIFE-THREATENING RISKS FROM USE OF FENTANYL ‎CITRATE INJECTION

See full prescribing information for complete boxed warning.

- Fentanyl Citrate Injection exposes users to risks of addiction, abuse, and misuse, which can lead to overdose and death. Assess patient's risk before prescribing and reassess regularly for these behaviors and conditions. (5.1)
- Serious, life-threatening, or fatal respiratory depression may occur with use Fentanyl Citrate Injection, especially during initiation or following a dosage increase. To reduce the risk of respiratory depression, proper dosing and titration of ‎Fentanyl Citrate Injection are essential.‎ (5.2)
- Concomitant use of opioids with benzodiazepines or other central nervous system (CNS) depressants, including alcohol, may result in profound sedation, respiratory depression, coma, and death. Reserve concomitant prescribing for use in patients for whom alternative treatment options are inadequate. (5.3, 7)
- Concomitant use with CYP3A4 inhibitors (or discontinuation of CYP3A4 inducers) can result in a fatal overdose of fentanyl. (5.4, 7, 12.3)

1 INDICATIONS AND USAGE

Fentanyl Citrate Injection is an opioid agonist indicated for (1):

- analgesic action of short duration during the anesthetic periods, premedication, induction and maintenance, and in the immediate postoperative period (recovery room) as the need arises.
- use as an opioid analgesic supplement in general or regional anesthesia.
- administration with a neuroleptic as an anesthetic premedication, for the induction of anesthesia and as an adjunct in the maintenance of general and regional anesthesia.
- use as an anesthetic agent with oxygen in selected high risk patients, such as those undergoing open heart surgery or certain complicated neurological or orthopedic procedures.

2 DOSAGE AND ADMINISTRATION

- Fentanyl Citrate Injection should be administered only by persons specifically trained in the use of intravenous anesthetics and management of the respiratory effects of potent opioids. (2.1)
- Ensure that an opioid overdose reversal agent, resuscitative and intubation equipment, and oxygen are readily available. (2.1)
- Individualize dosing based on the factors such as age, body weight, physical status, underlying pathological condition, use of other drugs, type of anesthesia to be used, and the surgical procedure involved. (2.1)
- Initiate treatment in adults with 50 to 100 mcg (0.05 to 0.1 mg) (1 to 2 mL). (2.2)
- Initiate treatment in children 2 to 12 years of age with a reduced dose as low as 2 to 3 mcg/kg. (2.2)

3 DOSAGE FORMS AND STRENGTHS

- Injection: 50 mcg (0.05 mg)/mL in single-dose Fliptop vial. (3)
- Injection: 50 mcg (0.05 mg)/mL in single-dose ampule. (3)

4 CONTRAINDICATIONS

- Hypersensitivity to fentanyl. (4)

5 WARNINGS AND PRECAUTIONS

- Risks of Skeletal Muscle Rigidity and Skeletal Muscle Movement: Manage with neuromuscular blocking agent. See full prescribing information for more detail on managing these risks. (5.5)
- Severe Cardiovascular Depression: Monitor during dosage initiation and titration. (5.6)
- Opioid-Induced Hyperalgesia and Allodynia: Opioid-Induced ‎Hyperalgesia (OIH) occurs when an opioid analgesic ‎paradoxically causes an increase in pain, or an increase in ‎sensitivity to pain. If OIH is suspected, carefully consider appropriately ‎decreasing the dose of the current opioid analgesic or ‎opioid rotation. (5.7)‎
- Serotonin Syndrome: Potentially life-threatening condition could result from concomitant serotonergic drug administration. Discontinue Fentanyl Citrate Injection if serotonin syndrome is suspected. (5.8)
- Adrenal Insufficiency: If diagnosed, treat with physiologic replacement of corticosteroids, and wean patient off of the opioid. (5.9)
- Risks of Use in Patients with Increased Intracranial Pressure, Brain Tumors, Head Injury, or Impaired Consciousness: Monitor for sedation and respiratory depression. (5.10)

6 ADVERSE REACTIONS

Most common serious adverse reactions were respiratory depression, apnea, rigidity, and bradycardia. (6)
To report SUSPECTED ADVERSE REACTIONS, contact Pfizer, Inc. at 1-800-438-1985, or FDA at 1-800-FDA-1088 or www.fda.gov/medwatch.

7 DRUG INTERACTIONS

- Concomitant Use of CNS Depressants: May decrease pulmonary arterial pressure and may cause hypotension. See FPI for management instructions. For post-operative pain, start with the lowest effective dosage and monitor for potentiation of CNS depressant effects. (5.3, 7)
- Mixed Agonist/Antagonist and Partial Agonist Opioid Analgesics: Avoid use with Fentanyl Citrate Injection because they may reduce analgesic effect of Fentanyl Citrate Injection or precipitate withdrawal symptoms. (7)

8 USE IN SPECIFIC POPULATIONS

- Pregnancy: May cause fetal harm. (8.1)
- Lactation: Infants exposed to Fentanyl Citrate Injection through breast milk should be monitored for excess sedation and respiratory depression. (8.2)
- Geriatric Patients: Titrate slowly and monitor for CNS and respiratory depression. (8.5)

FULL PRESCRIBING INFORMATION

WARNING: SERIOUS AND LIFE-THREATENING RISKS FROM USE OF FENTANYL ‎CITRATE INJECTION

Addiction, Abuse, and Misuse

Because the use of Fentanyl Citrate Injection exposes patients and other users to the risks of opioid addiction, abuse, and misuse, which can lead to overdose and death. Assess each patient’s risk prior to prescribing and reassess all patients regularly for the development of these behaviors and conditions [see Warnings and Precautions (5.1)].

Life-Threatening Respiratory Depression

Serious, life-threatening, or fatal respiratory depression may occur with use of Fentanyl Citrate Injection especially during initiation or following a dosage increase‎. To reduce the risk of respiratory depression, proper dosing and titration of Fentanyl Citrate Injection are essential [see Warnings and Precautions (5.2)].

Risks From Concomitant Use With Benzodiazepines Or Other CNS Depressants

Concomitant use of opioids with benzodiazepines or other central nervous system (CNS) depressants, including alcohol, may result in profound sedation, respiratory depression, coma, and death. Reserve concomitant prescribing of Fentanyl Citrate Injection and benzodiazepines or other CNS depressants for use in patients for whom alternative treatment options are inadequate [see Warnings and Precautions (5.3), Drug Interactions (7)].

Cytochrome P450 3A4 Interaction

The concomitant use of Fentanyl Citrate Injection with all cytochrome P450 3A4 inhibitors may result in an increase in fentanyl plasma concentrations, which could increase or prolong adverse reactions and may cause potentially fatal respiratory depression. In addition, discontinuation of a concomitantly used cytochrome P450 3A4 inducer may result in an increase in fentanyl plasma concentration. Monitor patients receiving Fentanyl Citrate Injection and any CYP3A4 inhibitor or inducer [see Warnings and Precautions (5.4), Drug Interactions (7), Clinical Pharmacology (12.3)].

1 INDICATIONS AND USAGE

Fentanyl Citrate Injection is indicated for:

- analgesic action of short duration during the anesthetic periods, premedication, induction and maintenance, and in the immediate postoperative period (recovery room) as the need arises.
- use as an opioid analgesic supplement in general or regional anesthesia.
- administration with a neuroleptic as an anesthetic premedication, for the induction of anesthesia and as an adjunct in the maintenance of general and regional anesthesia.
- use as an anesthetic agent with oxygen in selected high-risk patients, such as those undergoing open heart surgery or certain complicated neurological or orthopedic procedures.

2 DOSAGE AND ADMINISTRATION

2.1 Important Dosage and Administration Instructions

Fentanyl Citrate Injection should be administered only by persons specifically trained in the use of intravenous anesthetics and management of the respiratory effects of potent opioids.

- Ensure that an opioid overdose reversal agent (e.g., naloxone, nalmefene), resuscitative and intubation equipment, and oxygen are readily available.
- Individualize dosage based on factors such as age, body weight, physical status, underlying pathological condition, use of other drugs, type of anesthesia to be used, and the surgical procedure involved.
- Monitor vital signs routinely.

As with other potent opioids, the respiratory depressant effect of fentanyl may persist longer than the measured analgesic effect. The total dose of all opioid agonists administered should be considered by the practitioner before ordering opioid analgesics during recovery from anesthesia.

If Fentanyl Citrate Injection is administered with a CNS depressant, become familiar with the properties of each drug, particularly each product's duration of action. In addition, when such a combination is used, fluids and other countermeasures to manage hypotension should be available [see Warnings and Precautions (5.3)].

Inspect parenteral drug products visually for particulate matter and discoloration prior to administration, whenever solution and container permit.

2.2 Dosage

50 mcg = 0.05 mg = 1 mL

Premedication in Adults

50 to 100 mcg (0.05 to 0.1 mg) (1 to 2 mL) may be administered intramuscularly 30 to 60 minutes prior to surgery.

Adjunct to General Anesthesia

See Dosage Range Charts below.

Table 1: Dosage Range Chart
TOTAL DOSAGE (expressed as fentanyl base)
Low Dose – | Moderate Dose – | High Dose –
2 mcg/kg (0.002 mg/kg) (0.04 mL/kg). For use in minor, but painful, surgical procedures. May also provide some pain relief in the immediate postoperative period. | 2–20 mcg/kg (0.002–0.02 mg/kg) (0.04–0.4 mL/kg). For use in major surgical procedures, in addition to adequate analgesia, may abolish some of the stress response. Expect respiratory depression requiring artificial ventilation during anesthesia and careful observation of ventilation postoperatively is essential. | 20–50 mcg/kg (0.02–0.05 mg/kg) (0.4–1 mL/kg). For open heart surgery and certain more complicated neurosurgical and orthopedic procedures where surgery is more prolonged, and the stress response to surgery would be detrimental to the wellbeing of the patient. In conjunction with nitrous oxide/oxygen has been shown to attenuate the stress response as defined by increased levels of circulating growth hormone, catecholamine, ADH and prolactin. Expect the need for postoperative ventilation and observation are essential due to extended postoperative respiratory depression.
MAINTENANCE DOSE (expressed as fentanyl base)
Low Dose – | Moderate Dose – | High Dose –
2 mcg/kg (0.002 mg/kg) (0.04 mL/kg). Additional dosages are infrequently needed in these minor procedures. | 2–20 mcg/kg (0.002–0.02 mg/kg) (0.04–0.4 mL/kg). 25 to 100 mcg (0.025 to 0.1 mg) (0.5 to 2 mL) Administer intravenously or intramuscularly as needed when movement and/or changes in vital signs indicate surgical stress or lightening of analgesia. | 20–50 mcg/kg (0.02–0.05 mg/kg) (0.4–1 mL/kg). Maintenance dosage [ranging from 25 mcg (0.025 mg) (0.5 mL) to one half the initial loading dose] as needed based on vital signs changes indicative of stress and lightening of analgesia. Individualize dosage especially if the anticipated remaining operative time is short.

Adjunct to Regional Anesthesia

50 to 100 mcg (0.05 to 0.1 mg) (1 to 2 mL) may be administered intramuscularly or slowly intravenously, over one to two minutes, when additional analgesia is required.

Postoperatively (recovery room)

50 to 100 mcg (0.05 to 0.1 mg) (1 to 2 mL) may be administered intramuscularly for the control of pain, tachypnea and emergence delirium. The dose may be repeated in one to two hours as needed.

For Induction and Maintenance in Children 2 to 12 Years of Age

A reduced dose as low as 2 to 3 mcg/kg is recommended.

As a General Anesthetic

As a technique to attenuate the responses to surgical stress without the use of additional anesthetic agents, doses of 50 to 100 mcg/kg (0.05 to 0.1 mg/kg) (1 to 2 mL/kg) may be administered with oxygen and a muscle relaxant. In certain cases, doses up to 150 mcg/kg (0.15 mg/kg) (3 mL/kg) may be necessary to produce this anesthetic effect. It has been used for open heart surgery and certain other major surgical procedures in patients for whom protection of the myocardium from excess oxygen demand is particularly indicated, and for certain complicated neurological and orthopedic procedures.

3 DOSAGE FORMS AND STRENGTHS

- Injection: 50 mcg (0.05 mg)/mL in single-dose Fliptop vial.
- Injection: 50 mcg (0.05 mg)/mL in single-dose ampule.

4 CONTRAINDICATIONS

Fentanyl Citrate Injection is contraindicated in patients with:

- Hypersensitivity to fentanyl (e.g., anaphylaxis) [see Adverse Reactions (6)].

5 WARNINGS AND PRECAUTIONS

5.1 Addiction, Abuse, and Misuse

Fentanyl Citrate Injection contains fentanyl, a Schedule CII controlled substance. As an opioid, Fentanyl Citrate Injection exposes users to the risks of addiction, abuse, and misuse [see Drug Abuse and Dependence (9)].

Opioids are sought for nonmedical use and are subject to diversion from ‎legitimate prescribed use. Consider these risks when handling Fentanyl Citrate Injection. Strategies to reduce these risks include proper product storage and control practices for a C-II drug. Contact local state professional licensing board or state-controlled substances authority for information on how to prevent and detect abuse or diversion of this product.

5.2 Life-Threatening Respiratory Depression

Serious, life-threatening, or fatal respiratory depression has been reported with the use of opioids, even when used as recommended. Respiratory depression, if not immediately recognized and treated, may lead to respiratory arrest and death. Adequate facilities should be available for postoperative monitoring and ventilation of patients administered anesthetic doses of Fentanyl Citrate Injection. It is essential that these facilities be fully equipped to handle all degrees of respiratory depression. Management of respiratory depression may include close observation, supportive measures, and use of opioid overdose reversal agents (e.g., naloxone, nalmefene), depending on the patient's clinical status [see Overdosage (10)]. Carbon dioxide (CO2) retention from opioid-induced respiratory depression can exacerbate the sedating effects of opioids.

To reduce the risk of respiratory depression, proper dosing and titration of Fentanyl Citrate Injection are essential [see Dosage and Administration (2)]. As with other potent opioids, the respiratory depressant effect of fentanyl may persist longer than the measured analgesic effect. The total dose of all opioid agonists administered should be considered by the practitioner before ordering opioid analgesics during recovery from anesthesia.

Certain forms of conduction anesthesia, such as spinal anesthesia and some peridural anesthetics, can alter respiration by blocking intercostal nerves. Through other mechanisms [see Clinical Pharmacology (12.2)] Fentanyl Citrate Injection can also alter respiration. Therefore, when Fentanyl Citrate Injection is used to supplement these forms of anesthesia, the anesthetist should be familiar with the physiological alterations involved and be prepared to manage them in the patients selected for these forms of anesthesia.

Patients with significant chronic obstructive pulmonary disease or cor pulmonale, and those with a substantially decreased respiratory reserve, hypoxia, hypercapnia, or pre-existing respiratory depression are at increased risk of decreased respiratory drive including apnea, even at recommended dosages of Fentanyl Citrate Injection. Elderly, cachectic, or debilitated patients may have altered pharmacokinetics or altered clearance compared to younger, healthier patients resulting in greater risk for respiratory depression.

Monitor such patients closely including vital signs, particularly when initiating and titrating Fentanyl Citrate Injection and when Fentanyl Citrate Injection is given concomitantly with other drugs that depress respiration. To reduce the risk of respiratory depression, proper dosing and titration of Fentanyl Citrate Injection are essential [see Dosage and Administration (2)].

Opioids can cause sleep-related breathing disorders including central sleep apnea (CSA) and sleep-related hypoxemia. Opioid use increases the risk of CSA in a dose-dependent fashion. In patients who present with CSA, consider decreasing the opioid dosage using best practices for opioid taper [see Dosage and Administration (2.1)].

5.3 Risks from Concomitant Use with Benzodiazepines or Other Central Nervous System Depressants

When benzodiazepines or other CNS depressants are used with Fentanyl Citrate Injection, pulmonary arterial pressure may be decreased. This fact should be considered by those who conduct diagnostic and surgical procedures where interpretation of pulmonary arterial pressure measurements might determine final management of the patient. When high dose or anesthetic dosages of Fentanyl Citrate Injection are employed, even relatively small dosages of diazepam may cause cardiovascular depression.

When Fentanyl Citrate Injection is used with CNS depressants, hypotension can occur. If it occurs, consider the possibility of hypovolemia and manage with appropriate parenteral fluid therapy. When operative conditions permit, consider repositioning the patient to improve venous return to the heart. Exercise care in moving and repositioning of patients because of the possibility of orthostatic hypotension. If volume expansion with fluids plus other countermeasures do not correct hypotension, consider administration of pressor agents other than epinephrine. Epinephrine may paradoxically decrease blood pressure in patients treated with a neuroleptic that blocks alpha adrenergic activity.

Profound sedation, respiratory depression, coma, and death may result from the concomitant use of Fentanyl Citrate Injection with benzodiazepines and/or other CNS depressants‎, including alcohol‎ (e.g., non-benzodiazepine sedatives/hypnotics, anxiolytics, tranquilizers, muscle relaxants, general anesthetics, antipsychotics, gabapentinoids [gabapentin or pregabalin], and other opioids).

Observational studies have demonstrated that concomitant use of opioid analgesics and benzodiazepines increases the risk of drug-related mortality compared to use of opioid analgesics alone. Because of similar pharmacological properties, it is reasonable to expect similar risk with the concomitant use of other CNS depressant drugs with opioid analgesics [see Drug Interactions (7)].

If the decision is made to manage postoperative pain with Fentanyl Citrate Injection concomitantly with a benzodiazepine or other CNS depressant, start dosing with the lowest effective dosage and titrate based on clinical response. Monitor patients closely for signs and symptoms of respiratory depression, sedation, and hypotension. Fluids or other measures to counter hypotension should be available. [see Drug Interactions (7)].

5.4 Risks of Concomitant Use or Discontinuation of Cytochrome P450 3A4 Inhibitors and Inducers

Concomitant use of Fentanyl Citrate Injection with a CYP3A4 inhibitor, such as macrolide antibiotics (e.g., erythromycin), azole-antifungal agents (e.g., ketoconazole), and protease inhibitors (e.g., ritonavir), may increase plasma concentrations of fentanyl and prolong opioid adverse reactions, which may exacerbate respiratory depression [see Warnings and Precautions (5.2)], particularly when an inhibitor is added after a stable dose of Fentanyl Citrate Injection is achieved. Similarly, discontinuation of a CYP3A4 inducer, such as rifampin, carbamazepine, and phenytoin, in Fentanyl Citrate Injection-treated patients may increase fentanyl plasma concentrations and prolong opioid adverse reactions. When using Fentanyl Citrate Injection with CYP3A4 inhibitors or discontinuing CYP3A4 inducers in Fentanyl Citrate Injection-treated patients, monitor patients closely at frequent intervals and consider dosage reduction of Fentanyl Citrate Injection [see Dosage and Administration (2.1), Drug Interactions (7)].

Concomitant use of Fentanyl Citrate Injection with CYP3A4 inducers, or discontinuation of a CYP3A4 inhibitor, could result in lower than expected fentanyl plasma concentrations, decreased efficacy, or, possibly, lead to a withdrawal syndrome in a patient who had developed physical dependence to fentanyl. When using Fentanyl Citrate Injection with CYP3A4 inducers or discontinuation of a CYP3A4 inhibitor, monitor patients closely at frequent intervals and consider increasing the fentanyl dosage. [see Dosage and Administration (2.1), Drug Interactions (7)].

5.5 Risks of Muscle Rigidity and Skeletal Muscle Movement

Fentanyl Citrate Injection may cause muscle rigidity, particularly involving the muscles of respiration. The incidence and severity of muscle rigidity is dose related. These effects are related to the dose and speed of injection. Skeletal muscle rigidity also has been reported to occur or recur infrequently in the extended postoperative period usually following high dose administration. In addition, skeletal muscle movements of various groups in the extremities, neck, and external eye have been reported during induction of anesthesia with Fentanyl Citrate Injection; these reported movements have, on rare occasions, been strong enough to pose patient management problems.

These effects are related to the dose and speed of injection and its incidence can be reduced by: 1) administration of up to 1/4 of the full paralyzing dose of a non-depolarizing neuromuscular blocking agent just prior to administration of Fentanyl Citrate Injection; 2) administration of a full paralyzing dose of a neuromuscular blocking agent following loss of eyelash reflex when Fentanyl Citrate Injection is used in anesthetic doses titrated by slow intravenous infusion; or, 3) simultaneous administration of Fentanyl Citrate Injection and a full paralyzing dose of a neuromuscular blocking agent when Fentanyl Citrate Injection is used in rapidly administered anesthetic dosages. The neuromuscular blocking agent used should be compatible with the patient's cardiovascular status.

5.6 Severe Cardiovascular Depression

Fentanyl Citrate Injection may cause severe bradycardia, severe hypotension including orthostatic hypotension, and syncope. There is increased risk in patients whose ability to maintain blood pressure has already been compromised by a reduced blood volume or concurrent administration of certain CNS depressant drugs (e.g., phenothiazines or general anesthetics) [see Drug Interactions (7)]. In patients with circulatory shock, Fentanyl Citrate Injection may cause vasodilation that can further reduce cardiac output and blood pressure. Monitor these patients for signs of hypotension after initiating or titrating the dosage of Fentanyl Citrate Injection.

5.7 Opioid-Induced Hyperalgesia and Allodynia

Opioid-Induced Hyperalgesia (OIH) occurs when an opioid analgesic ‎paradoxically causes an increase in pain, or an increase in sensitivity to pain. ‎This condition differs from tolerance, which is the need for increasing doses of ‎opioids to maintain a defined effect [see Drug Abuse and Dependence (9.3)]. Symptoms of OIH ‎include (but may not be limited to) increased levels of pain upon opioid dosage ‎increase, decreased levels of pain upon opioid dosage decrease, or pain from ‎ordinarily non-painful stimuli (allodynia). These symptoms may suggest OIH only ‎if there is no evidence of underlying disease progression, opioid tolerance, ‎opioid withdrawal, or addictive behavior.‎

Cases of OIH have been reported, both with short-term and longer-term use of ‎opioid analgesics. Though the mechanism of OIH is not fully understood, ‎multiple biochemical pathways have been implicated. Medical literature suggests ‎a strong biologic plausibility between opioid analgesics and OIH and allodynia. If ‎a patient is suspected to be experiencing OIH, carefully consider appropriately ‎decreasing the dose of the current opioid analgesic or opioid rotation (safely ‎switching the patient to a different opioid moiety) [see Dosage and ‎Administration (2), Warnings and Precautions (5.7)].‎

5.8 Serotonin Syndrome with Concomitant Use of Serotonergic Drugs

Cases of serotonin syndrome, a potentially life-threatening condition, have been reported during concomitant use of fentanyl with serotonergic drugs. Serotonergic drugs include selective serotonin reuptake inhibitors (SSRIs), serotonin and norepinephrine reuptake inhibitors (SNRIs), tricyclic antidepressants (TCAs), triptans, 5-HT3 receptor antagonists, drugs that affect the serotonergic neurotransmitter system (e.g., mirtazapine, trazodone, tramadol), certain muscle relaxants (i.e., cyclobenzaprine, metaxalone), and drugs that impair metabolism of serotonin (including MAO inhibitors, both those intended to treat psychiatric disorders and also others, such as linezolid and intravenous methylene blue) [see Drug Interactions (7)]. This may occur within the recommended dosage range.

Serotonin syndrome symptoms may include mental status changes (e.g., agitation, hallucinations, coma), autonomic instability (e.g., tachycardia, labile blood pressure, hyperthermia), neuromuscular aberrations (e.g., hyperreflexia, incoordination, rigidity), and/or gastrointestinal symptoms (e.g., nausea, vomiting, diarrhea) and can be fatal. The onset of symptoms generally occurs within several hours to a few days of concomitant use but may occur later than that. Discontinue Fentanyl Citrate Injection if serotonin syndrome is suspected.

5.9 Adrenal Insufficiency

Cases of adrenal insufficiency have been reported with opioid use, more often following greater than one month of use. Presentation of adrenal insufficiency may include non-specific symptoms and signs including nausea, vomiting, anorexia, fatigue, weakness, dizziness, and low blood pressure. If adrenal insufficiency is suspected, confirm the diagnosis with diagnostic testing as soon as possible. If adrenal insufficiency is diagnosed, treat with physiologic replacement doses of corticosteroids. Wean the patient off of the opioid to allow adrenal function to recover and continue corticosteroid treatment until adrenal function recovers. Other opioids may be tried as some cases reported use of a different opioid without recurrence of adrenal insufficiency. The information available does not identify any particular opioids as being more likely to be associated with adrenal insufficiency.

5.10 Risks of Use in Patients with Increased Intracranial Pressure, Brain Tumors, Head Injury or Impaired Consciousness

In patients who may be susceptible to the intracranial effects of CO2 retention (e.g., those with evidence of increased intracranial pressure or brain tumors), Fentanyl Citrate Injection may reduce respiratory drive, and the resultant CO2 retention can further increase intracranial pressure. Monitor such patients for worsening of signs of increasing intracranial pressure. Monitor patients for signs of sedation and respiratory depression, particularly when initiating therapy with Fentanyl Citrate Injection.

Opioids may also obscure the clinical course in a patient with a head injury. Avoid the use of Fentanyl Citrate Injection in patients with impaired consciousness or coma.

5.11 Risks of Gastrointestinal Complications

Fentanyl may cause spasm of the sphincter of Oddi. Opioids may cause increases in serum amylase. Monitor patients with biliary tract disease, including acute pancreatitis for worsening symptoms.

Cases of opioid-induced esophageal dysfunction (OIED) have been reported in patients taking opioids. The risk of OIED may increase as the dose and/or duration of opioids increases. Regularly evaluate patients for signs and symptoms of OIED (e.g., dysphagia, regurgitation, non-cardiac chest pain) and, if necessary, adjust opioid therapy as clinically appropriate [see Clinical Pharmacology (12.2)].

5.12 Increased Risk of Seizures in Patients with Seizure Disorders

Fentanyl may increase the frequency of seizures in patients with seizure disorders, and may increase the risk of seizures occurring in other clinical settings associated with seizures. Monitor patients with a history of seizure disorders for worsened seizure control during Fentanyl Citrate Injection therapy.

5.13 Risks of Driving and Operating Machinery

Fentanyl may impair the mental or physical abilities needed to perform potentially hazardous activities such as driving a car or operating machinery. Warn patients not to drive or operate dangerous machinery after Fentanyl Citrate Injection administration.

5.14 Risks due to Interaction with Neuroleptic Agents

Many neuroleptic agents have been associated with QT prolongation, torsades de pointes, and cardiac arrest. Administer neuroleptic agents with extreme caution in the presence of risk factors for development of prolonged QT syndrome and torsades de pointes, such as: 1) clinically significant bradycardia (less than 50 bpm), 2) any clinically significant cardiac disease, including baseline prolonged QT interval, 3) treatment with Class 1 and Class III antiarrhythmics, 4) treatment with monoamine oxidase inhibitors (MAOI's), 5) concomitant treatment with other drug products known to prolong the QT interval and 6) electrolyte imbalance, in particular hypokalemia and hypomagnesemia, or concomitant treatment with drugs (e.g., diuretics) that may cause electrolyte imbalance.

Elevated blood pressure, with and without pre-existing hypertension, has been reported following administration of Fentanyl Citrate Injection combined with a neuroleptic. This might be due to unexplained alterations in sympathetic activity following large doses; however, it is also frequently attributed to anesthetic and surgical stimulation during light anesthesia.

ECG monitoring is indicated when a neuroleptic agent is used in conjunction with Fentanyl Citrate Injection as an anesthetic premedication, for the induction of anesthesia, or as an adjunct in the maintenance of general or regional anesthesia.

When Fentanyl Citrate Injection is used with a neuroleptic and an EEG is used for postoperative monitoring, the EEG pattern may return to normal slowly.

6 ADVERSE REACTIONS

The following serious adverse reactions are described, or described in greater detail, in other sections:

- Addiction, Abuse, and Misuse [see Warnings and Precautions (5.1)]
- Life-Threatening Respiratory Depression [see Warnings and Precautions (5.2)]
- Interactions with Benzodiazepines or Other CNS Depressants [see Warnings and Precautions (5.3)]
- Severe Cardiovascular Depression [see Warnings and Precautions (5.6)]
- Opioid-Induced Hyperalgesia and Allodynia [see Warnings and Precautions (5.7)]‎
- Serotonin Syndrome [see Warnings and Precautions (5.8)]
- Gastrointestinal Adverse Reactions [see Warnings and Precautions (5.11)]
- Seizures [see Warnings and Precautions (5.12)]

The following adverse reactions associated with the use of fentanyl were identified in clinical studies or postmarketing reports. Because some of these reactions were reported voluntarily from a population of uncertain size, it is not always possible to reliably estimate their frequency or establish a causal relationship to drug exposure.

As with other opioid agonists, the most common serious adverse reactions reported to occur with fentanyl are respiratory depression, apnea, rigidity, and bradycardia; if these remain untreated, respiratory arrest, circulatory depression or cardiac arrest could occur. Other adverse reactions that have been reported are hypertension, hypotension, dizziness, blurred vision, nausea, emesis, diaphoresis, pruritus, urticarial, laryngospasm, and anaphylaxis.

It has been reported that secondary rebound respiratory depression may occasionally occur postoperatively.

When a tranquilizer is used with fentanyl, the following adverse reactions can occur: chills and/or shivering, restlessness, and postoperative hallucinatory episodes (sometimes associated with transient periods of mental depression); extrapyramidal symptoms (dystonia, akathisia, and oculogyric crisis) have been observed up to 24 hours postoperatively. When they occur, extrapyramidal symptoms can usually be controlled with anti-parkinson agents. Postoperative drowsiness is also frequently reported following the use of neuroleptics with Fentanyl Citrate Injection.

Cases of cardiac dysrhythmias, cardiac arrest, and death have been reported following the use of Fentanyl Citrate Injection with a neuroleptic agent.

Serotonin syndrome: Cases of serotonin syndrome, a potentially life-threatening condition, have been reported during concomitant use of opioids with serotonergic drugs.

Adrenal insufficiency: Cases of adrenal insufficiency have been reported with opioid use, more often following greater than one month of use.

Anaphylaxis: Anaphylaxis has been reported with ingredients contained in Fentanyl Citrate Injection.

Androgen deficiency: Cases of androgen deficiency have occurred with use of opioids for an extended period of time [see Clinical Pharmacology (12.2)].

Hyperalgesia and Allodynia: Cases of hyperalgesia and allodynia have been ‎reported with opioid therapy of any duration [see Warnings and Precautions ‎‎(5.7)]‎.

Hypoglycemia: Cases of hypoglycemia have been reported in patients ‎taking opioids. Most reports were in ‎patients with at least one ‎predisposing risk factor (e.g., diabetes).

Opioid-induced esophageal dysfunction (OIED): Cases of OIED have been reported in patients taking opioids and may occur more frequently in patients taking higher doses of opioids, and/or in patients taking opioids longer term [see Warnings and Precautions (5.11)].

7 DRUG INTERACTIONS

Table 2 includes clinically significant drug interactions with Fentanyl Citrate Injection.

Table 2: Clinically Significant Drug Interactions with Fentanyl Citrate Injection
Inhibitors of CYP3A4
Clinical Impact: | The concomitant use of Fentanyl Citrate Injection and CYP3A4 inhibitors can increase the plasma concentration of fentanyl, resulting in increased or prolonged opioid effects, particularly when an inhibitor is added after a stable dose of Fentanyl Citrate Injection is achieved [see Warnings and Precautions (5.4)]. After stopping a CYP3A4 inhibitor, as the effects of the inhibitor decline, the fentanyl plasma concentration will decrease [see Clinical Pharmacology (12.3)], resulting in decreased opioid efficacy or a withdrawal syndrome in patients who had developed physical dependence to fentanyl.
Intervention: | If concomitant use is necessary, consider dosage reduction of Fentanyl Citrate Injection until stable drug effects are achieved [see Dosage and Administration (2)]. Monitor patients for respiratory depression and sedation at frequent intervals. If a CYP3A4 inhibitor is discontinued, consider increasing the Fentanyl Citrate Injection dosage until stable drug effects are achieved. Monitor for signs of opioid withdrawal.
Examples: | Macrolide antibiotics (e.g., erythromycin), azole-antifungal agents (e.g., ketoconazole), protease inhibitors (e.g., ritonavir), grapefruit juice.
CYP3A4 Inducers
Clinical Impact: | The concomitant use of Fentanyl Citrate Injection and CYP3A4 inducers can decrease the plasma concentration of fentanyl [see Clinical Pharmacology (12.3)], resulting in decreased efficacy or onset of a withdrawal syndrome in patients who have developed physical dependence to fentanyl [see Warnings and Precautions (5.4)]. After stopping a CYP3A4 inducer, as the effects of the inducer decline, the fentanyl plasma concentration will increase [see Clinical Pharmacology (12.3)], which could increase or prolong both the therapeutic effects and adverse reactions and may cause serious respiratory depression.
Intervention: | If concomitant use is necessary, consider increasing the Fentanyl Citrate Injection dosage until stable drug effects are achieved. Monitor for signs of opioid withdrawal. If a CYP3A4 inducer is discontinued, consider Fentanyl Citrate Injection dosage reduction and monitor for signs of respiratory depression.
Examples: | Rifampin, carbamazepine, phenytoin
Benzodiazepines and Other Central Nervous System (CNS) Depressants
Clinical Impact: | The concomitant use of Fentanyl Citrate Injection with CNS depressants may result in decreased pulmonary artery pressure and may cause hypotension. Even small dosages of diazepam may cause cardiovascular depression when added to high dose or anesthetic dosages of Fentanyl Citrate Injection. As postoperative analgesia, concomitant use of Fentanyl Citrate Injection can increase the risk of hypotension, respiratory depression, profound sedation, coma, and death.
Intervention: | As postoperative analgesia, start with a lower dose of Fentanyl Citrate Injection and monitor patients for signs of respiratory depression, sedation, and hypotension. Fluids or other measures to counter hypotension should be available. [see Warnings and Precautions (5.3)].
Examples: | Benzodiazepines and other sedatives/hypnotics, anxiolytics, tranquilizers, muscle relaxants, general anesthetics, antipsychotics, gabapentinoids (gabapentin or pregabalin), other opioids, alcohol.
Serotonergic Drugs
Clinical Impact: | The concomitant use of opioids with other drugs that affect the serotonergic neurotransmitter system has resulted in serotonin syndrome [see Warnings and Precautions (5.8)].
Intervention: | If concomitant use is warranted, carefully observe the patient, particularly during treatment initiation and dose adjustment. Discontinue Fentanyl Citrate Injection if serotonin syndrome is suspected.
Examples: | Selective serotonin reuptake inhibitors (SSRIs), serotonin and norepinephrine reuptake inhibitors (SNRIs), tricyclic antidepressants (TCAs), triptans, 5-HT3 receptor antagonists, drugs that effect the serotonin neurotransmitter system (e.g., mirtazapine, trazodone, tramadol), certain muscle relaxants (i.e., cyclobenzaprine, metaxalone), monoamine oxidase (MAO) inhibitors (those intended to treat psychiatric disorders and also others, such as linezolid and intravenous methylene blue).
Monoamine Oxidase Inhibitors
Clinical Impact: | MAOI interactions with opioids may manifest as serotonin syndrome [see Warnings and Precautions (5.8)] or opioid toxicity (e.g., respiratory depression, coma) [see Warnings and Precautions (5.2)]
Intervention: | The use of Fentanyl Citrate Injection is not recommended for patients taking MAOIs or within 14 days of stopping such treatment.
Examples: | Phenelzine, tranylcypromine, linezolid
Mixed Agonist/Antagonist and Partial Agonist Opioid Analgesics
Clinical Impact: | May reduce the analgesic effect of Fentanyl Citrate Injection and/or precipitate withdrawal symptoms.
Intervention: | Avoid concomitant use.
Examples: | Butorphanol, nalbuphine, pentazocine, buprenorphine.
Muscle Relaxants
Clinical Impact: | Fentanyl may enhance the neuromuscular blocking action of skeletal muscle relaxants and produce an increased degree of respiratory depression.
Intervention: | Monitor patients for signs of respiratory depression that may be greater than otherwise expected and decrease the dosage of Fentanyl Citrate Injection and/or the muscle relaxant as necessary.
Examples: | Cyclobenzaprine, metaxalone.
Diuretics
Clinical Impact: | Opioids can reduce the efficacy of diuretics by inducing the release of antidiuretic hormone.
Intervention: | Monitor patients for signs of diminished diuresis and/or effects on blood pressure and increase the dosage of the diuretic as needed.
Anticholinergic Drugs
Clinical Impact: | The concomitant use of anticholinergic drugs may increase risk of urinary retention and/or severe constipation, which may lead to paralytic ileus.
Intervention: | Monitor patients for signs of urinary retention or reduced gastric motility when Fentanyl Citrate Injection is used concomitantly with anticholinergic drugs.
Neuroleptics
Clinical Impact: | Elevated blood pressure, with and without pre-existing hypertension, has been reported following administration of Fentanyl Citrate Injection combined with a neuroleptic [see Warnings and Precautions (5.14)].
Intervention: | ECG monitoring is indicated when a neuroleptic agent is used in conjunction with Fentanyl Citrate Injection as an anesthetic premedication, for the induction of anesthesia, or as an adjunct in the maintenance of general or regional anesthesia.
Nitrous oxide
Clinical Impact: | Nitrous oxide has been reported to produce cardiovascular depression when given with higher doses of Fentanyl Citrate Injection.
Intervention: | Monitor patients for signs of cardiovascular depression that may be greater than otherwise expected.

8 USE IN SPECIFIC POPULATIONS

8.1 Pregnancy

Risk Summary

Use of opioid analgesics for an extended period of time during pregnancy may cause Neonatal Opioid Withdrawal Syndrome. Available data with Fentanyl Citrate Injection in pregnant women are insufficient to inform a drug‑associated risk for major birth defects and miscarriage ‎or adverse maternal outcomes‎. There are adverse outcomes reported with fetal exposure to opioid analgesics [see Clinical ‎Considerations].‎

In animal reproduction studies, fentanyl administration to pregnant rats during organogenesis was embryocidal at doses within the range of the human recommended dosing. No evidence of malformations was noted in animal studies completed to date [see Data]. The estimated background risk of major birth defects and miscarriage for the indicated population is unknown. All pregnancies have a background risk of birth defect, loss, or other adverse outcomes.

The background risk of major birth defects and miscarriage for the indicated population is unknown. All ‎pregnancies have a background risk of birth defect, loss, or other adverse outcomes.‎ In the U.S. general population, the estimated background risk of major birth defects and miscarriage in clinically recognized pregnancies is 2 to 4% and 15 to 20%, respectively.

Clinical Considerations

Fetal/Neonatal Adverse Reactions

Use of opioid analgesics for an extended period of time during pregnancy for medical or nonmedical purposes can result in physical dependence in the neonate and neonatal opioid withdrawal syndrome shortly after birth.

Neonatal opioid withdrawal syndrome presents as irritability, hyperactivity and abnormal sleep pattern, high pitched cry, tremor, vomiting, diarrhea and failure to gain weight. The onset, duration, and severity of neonatal opioid withdrawal syndrome vary based on the specific opioid used, duration of use, timing and amount of last maternal use, and rate of elimination of the drug by the newborn. Observe newborns for symptoms of neonatal opioid withdrawal syndrome and manage accordingly.

Labor or Delivery

Opioids cross the placenta and may produce respiratory depression and psycho-physiologic effects in neonates. An opioid overdose reversal agent, such as naloxone or nalmefene, must be available for reversal of opioid-induced respiratory depression in the neonate. Fentanyl Citrate Injection is not recommended for use in pregnant women during or immediately prior to labor, when other analgesic techniques are more appropriate. Opioid analgesics, including Fentanyl Citrate Injection, can prolong labor through actions which temporarily reduce the strength, duration, and frequency of uterine contractions. However, this effect is not consistent and may be offset by an increased rate of cervical dilation, which tends to shorten labor. Monitor neonates exposed to opioid analgesics during labor for signs of excess sedation and respiratory depression.

Data

Animal Data

Fentanyl has been shown to embryocidal in pregnant rats at doses of 30 mcg/kg intravenously (0.05 times the human dose of 100 mcg/kg on a mg/m^2 basis) and 160 mcg/kg subcutaneously (0.26 times the human dose of 100 mcg/kg on a mg/m^2 basis). There was no evidence of teratogenicity reported.

No evidence of malformations or adverse effects on the fetus was reported in a published study in which pregnant rats were administered fentanyl continuously via subcutaneously implanted osmotic minipumps at doses of 10, 100, or 500 mcg/kg/day starting 2-weeks prior to breeding and throughout pregnancy. The high dose was approximately 0.81 times the human dose of 100 mcg/kg on a mg/m^2 basis.

8.2 Lactation

Risk Summary

Fentanyl is present in breast milk. However, there is insufficient information to determine the effects of fentanyl on the breastfed infant and the effects of fentanyl on milk production.

The developmental and health benefits of breastfeeding should be considered along with the mother's clinical need for Fentanyl Citrate Injection and any potential adverse effects on the breastfed infant from Fentanyl Citrate Injection or from the underlying maternal condition.

Clinical Considerations

Monitor infants exposed to Fentanyl Citrate Injection through breast milk for excess sedation and respiratory depression. Withdrawal symptoms can occur in breastfed infants when maternal administration of an opioid analgesic is stopped, or when breast-feeding is stopped.

8.3 Females and Males of Reproductive Potential

Infertility

Use of opioids for an extended period of time may cause reduced fertility in females and males of reproductive potential. It is not known whether these effects on fertility are reversible [see Adverse Reactions (6), Clinical Pharmacology (12.2), Nonclinical Toxicology (13.1)].

8.4 Pediatric Use

The safety and efficacy of Fentanyl Citrate Injection in children under two years of age has not been established.

Rare cases of unexplained clinically significant methemoglobinemia have been reported in premature neonates undergoing emergency anesthesia and surgery which included the combined use of fentanyl, pancuronium and atropine. A direct cause and effect relationship between the combined use of these drugs and the reported cases of methemoglobinemia has not been established.

8.5 Geriatric Use

Elderly patients (aged 65 years or older) may have increased sensitivity to fentanyl. In general, use caution when selecting a dosage for an elderly patient, usually starting at the low end of the dosing range, reflecting the greater frequency of decreased hepatic, renal, or cardiac function and of concomitant disease or other drug therapy.

Respiratory depression is the chief risk for elderly patients treated with opioids and has occurred after large initial doses were administered to patients who were not opioid-tolerant or when opioids were co-administered with other agents that depress respiration. Titrate the dosage of Fentanyl Citrate Injection slowly in geriatric patients and monitor closely for signs of central nervous system and respiratory depression [see Warnings and Precautions (5.2)].

Fentanyl is known to be substantially excreted by the kidney, and the risk of adverse reactions to this drug may be greater in patients with impaired renal function. Because elderly patients are more likely to have decreased renal function, care should be taken in dose selection, and it may be useful to monitor renal function.

8.6 Hepatic Impairment

Fentanyl Citrate Injection should be administered with caution to patients with liver dysfunction because of the extensive hepatic metabolism. Reduce the dosage as needed and monitor closely for signs of respiratory depression, sedation, and hypotension.

8.7 Renal Impairment

Fentanyl Citrate Injection should be administered with caution to patients with kidney dysfunction because of the renal excretion of fentanyl and its metabolites. Reduce the dosage as needed and monitor for signs of respiratory depression, sedation, and hypotension.

9 DRUG ABUSE AND DEPENDENCE

9.1 Controlled Substance

Fentanyl Citrate Injection contains fentanyl, a Schedule II controlled substance.

9.2 Abuse

Fentanyl Citrate Injection contains fentanyl, a substance with high potential for misuse and abuse, which can lead to the development of ‎substance use disorder, including addiction [see Warnings and Precautions (5.1)].

Misuse is the intentional use, for therapeutic purposes, of a drug by an ‎individual in a way other than prescribed by a healthcare provider or for ‎whom it was not prescribed.‎

Abuse is the intentional, non-therapeutic use of a drug, even once, for its desirable psychological or physiological effects.

Drug addiction is a cluster of behavioral, cognitive, and physiological phenomena that may include a strong desire to take the drug, difficulties in controlling drug use (e.g., continuing drug use despite harmful ‎consequences, giving a higher priority to drug use than other activities and ‎obligations), and possible tolerance or physical dependence.‎

Misuse and abuse of Fentanyl Citrate Injection increases risk of ‎overdose, which may lead to central nervous system and respiratory ‎depression, hypotension, seizures, and death. The risk is increased with ‎concurrent abuse of Fentanyl Citrate Injection with alcohol and/or other ‎CNS depressants. Abuse of and addiction to opioids in ‎some individuals may not be accompanied by concurrent tolerance and ‎symptoms of physical dependence. In addition, abuse of opioids can ‎occur in the absence of addiction.‎

All patients treated with opioids require careful and frequent reevaluation ‎for signs of misuse, abuse, and addiction, because use of opioid analgesic ‎products carries the risk of addiction even under appropriate medical use. ‎Patients at high risk of Fentanyl Citrate Injection abuse include those with ‎a history of prolonged use of any opioid, including products containing fentanyl, those with a ‎history of drug or alcohol abuse, or those who use Fentanyl Citrate ‎Injection in combination with other abused drugs.‎

‎“Drug-seeking” behavior is very common in persons with substance use ‎disorders. Drug-seeking tactics include emergency calls or visits near the ‎end of office hours, refusal to undergo appropriate examination, testing, or ‎referral, repeated “loss” of prescriptions, tampering with prescriptions, ‎and reluctance to provide prior medical records or contact information for ‎other treating healthcare provider(s). “Doctor shopping” (visiting multiple ‎prescribers to obtain additional prescriptions) is common among people ‎who abuse drugs and people with substance use disorder. Preoccupation ‎with achieving adequate pain relief can be appropriate behavior in a ‎patient with inadequate pain control.‎

Fentanyl Citrate Injection, like other opioids, can be diverted for nonmedical use into illicit channels of distribution. Careful record-keeping of prescribing information, including quantity, frequency, and renewal requests, as required by state and federal law, is strongly advised.

Proper assessment of the patient, proper prescribing practices, periodic reevaluation of therapy, and proper dispensing and storage are appropriate measures that help to limit abuse of opioid drugs.

Risks Specific to Abuse of Fentanyl Citrate Injection

Abuse of Fentanyl Citrate Injection poses a risk of overdose and death. The risk is increased with concurrent use of Fentanyl Citrate Injection with alcohol and/or other CNS depressants.

Parenteral drug abuse is commonly associated with transmission of infectious diseases such as hepatitis and HIV.

9.3 Dependence

Both tolerance and physical dependence can develop during use of opioid therapy.

Tolerance is a physiological state characterized by a reduced response to ‎a drug after repeated administration (i.e., a higher dose of a drug is ‎required to produce the same effect that was once obtained at a lower ‎dose).‎

Physical dependence is a state that develops as a result of a ‎physiological adaptation in response to repeated drug use, manifested by ‎withdrawal signs and symptoms after abrupt discontinuation or a ‎significant dose reduction of a drug.‎

Withdrawal may be precipitated through the administration of drugs with opioid antagonist activity (e.g., naloxone, nalmefene), mixed agonist/antagonist analgesics (e.g., pentazocine, butorphanol, nalbuphine), or partial agonists (e.g., buprenorphine). Physical dependence may not occur to a clinically significant degree until after several days to weeks of continued use.

Fentanyl Citrate Injection should not be rapidly reduced or abruptly discontinued in a ‎physically-dependent patient. If Fentanyl Citrate Injection is rapidly reduced or abruptly ‎discontinued in a physically-dependent patient, a withdrawal syndrome ‎may occur, typically characterized by restlessness, lacrimation, rhinorrhea, ‎perspiration, chills, myalgia, and mydriasis. Other signs and symptoms ‎also may develop, including irritability, anxiety, backache, joint pain, ‎weakness, abdominal cramps, insomnia, nausea, anorexia, vomiting, ‎diarrhea, or increased blood pressure, respiratory rate, or heart rate.‎

Infants born to mothers physically-dependent on opioids will also be ‎physically-dependent and may exhibit respiratory difficulties and ‎withdrawal signs [see Use in Specific Populations (8.1)].‎

10 OVERDOSAGE

Clinical Presentation

Acute overdose with fentanyl can be manifested by respiratory depression, somnolence progressing to stupor or coma, skeletal muscle flaccidity, cold and clammy skin, constricted pupils, and in some cases, pulmonary edema, bradycardia, hypotension, hypoglycemia, partial or complete airway obstruction, atypical snoring, and death. Marked mydriasis rather than miosis may be seen with hypoxia in overdose situations [see Clinical Pharmacology (12.2)]. Toxic leukoencephalopathy has been reported after opioid overdose and can present hours, days, or weeks after apparent recovery from the initial intoxication.

Treatment of Overdose

In case of overdose, priorities are the reestablishment of a patent and protected airway and institution of assisted or controlled ventilation, if needed. Employ other supportive measures (including oxygen and vasopressors) in the management of circulatory shock and pulmonary edema as indicated. Cardiac arrest or arrhythmias will require advanced life-support measures.

For clinically significant respiratory or circulatory depression secondary to fentanyl overdose, administer an opioid overdose reversal agent such as naloxone or nalmefene.

Because the duration of opioid reversal is expected to be less than the duration of action of fentanyl in Fentanyl Citrate Injection, carefully monitor the patient until spontaneous respiration is reliably re-established. If the response to an opioid overdose reversal agent is suboptimal or only brief in nature, administer additional reversal agent as directed by the product's prescribing information.

In an individual physically-dependent on opioids, administration of the recommended usual dosage of the opioid overdose reversal agent will precipitate an acute withdrawal syndrome. The severity of the withdrawal symptoms experienced will depend on the degree of physical dependence and the dose of the reversal agent administered. If a decision is made to treat serious respiratory depression in the physically-dependent patient, administration of the reversal agent should be initiated with care and by titration with smaller than usual doses of the reversal agent.

11 DESCRIPTION

Fentanyl Citrate Injection is an opioid agonist. Fentanyl Citrate Injection, is a sterile, nonpyrogenic solution of fentanyl citrate in water for injection, available as 50 mcg (0.05 mg) per mL which is administered only by the intravenous or intramuscular routes of injection. The chemical name is N-(1-phenethyl-4-piperidyl) propionanilide citrate (1:1). The molecular weight is 528.60. Its molecular formula is C22H28N2O∙C6H8O7, and it has the following chemical structure.

Fentanyl citrate, a white powder which is sparingly soluble in water. Each milliliter contains fentanyl (as the citrate) 50 mcg (0.05 mg). May contain sodium hydroxide and/or hydrochloric acid for pH adjustment. pH 4.7 (4.0 to 7.5).

The solution contains no bacteriostat, antimicrobial agent or added buffer and is intended only for use as a single-dose injection. When smaller doses are required, the unused portion should be discarded in an appropriate manner.

12 CLINICAL PHARMACOLOGY

12.1 Mechanism of Action

Fentanyl is an opioid agonist whose principal actions of therapeutic value are analgesic and sedation.

12.2 Pharmacodynamics

Effects on the Central Nervous System

Fentanyl produces respiratory depression by direct action on brain stem respiratory centers. The respiratory depression involves a reduction in the responsiveness of the brain stem respiratory centers to both increases in carbon dioxide tension and electrical stimulation.

Fentanyl causes miosis, even in total darkness. Pinpoint pupils are a sign of opioid overdose but are not pathognomonic (e.g., pontine lesions of hemorrhagic or ischemic origins may produce similar findings). Marked mydriasis rather than miosis may be seen due to hypoxia in overdose situations.

Effects on the Gastrointestinal Tract and Other Smooth Muscle

Fentanyl causes a reduction in motility associated with an increase in smooth muscle tone in the antrum of the stomach and duodenum. Digestion of food in the small intestine is delayed and propulsive contractions are decreased. Propulsive peristaltic waves in the colon are decreased, while tone may be increased to the point of spasm resulting in constipation. Other opioid-induced effects may include a reduction in biliary and pancreatic secretions, spasm of sphincter of Oddi, transient elevations in serum amylase, and opioid-induced esophageal dysfunction (OIED).

Effects on the Cardiovascular System

Fentanyl produces peripheral vasodilation which may result in orthostatic hypotension or syncope. Manifestations of histamine release and/or peripheral vasodilation may include pruritus, flushing, red eyes, sweating, and/or orthostatic hypotension.

Effects on the Endocrine System

Opioids inhibit the secretion of adrenocorticotropic hormone (ACTH), cortisol, and luteinizing hormone (LH) in humans [see Adverse Reactions (6)]. They also stimulate prolactin, growth hormone (GH) secretion, and pancreatic secretion of insulin and glucagon.

Use of opioids for an extended period of time may influence the hypothalamic-pituitary-gonadal axis, leading to androgen deficiency that may manifest as low libido, impotence, erectile dysfunction, amenorrhea, or infertility. The causal role of opioids in the clinical syndrome of hypogonadism is unknown because the various medical, physical, lifestyle, and psychological stressors that may influence gonadal hormone levels have not been adequately controlled for in studies conducted to date [see Adverse Reactions (6)].

Effects on the Immune System

Opioids have been shown to have a variety of effects on components of the immune system in in vitro and animal models. The clinical significance of these findings is unknown. Overall, the effects of opioids appear to be modestly immunosuppressive.

Concentration–Efficacy Relationships

A dose of 100 mcg (0.1 mg) (2.0 mL) of Fentanyl Citrate Injection is approximately equivalent in analgesic activity to 10 mg of morphine or 75 mg of meperidine.

The minimum effective analgesic concentration will vary widely among patients, especially among patients who have been previously treated with opioid agonists. The minimum effective analgesic concentration of fentanyl for any individual patient may increase over time due to an increase in pain, the development of a new pain syndrome and/or the development of analgesic tolerance [see Dosage and Administration (2.1, 2.2)].

The onset of action of fentanyl is almost immediate when the drug is given intravenously; however, the maximal analgesic effect may not be noted for several minutes. The usual duration of action of the analgesic effect is 30 to 60 minutes after a single intravenous dose of up to 100 mcg (0.1 mg) (2 mL). Following intramuscular administration, the onset of action is from seven to eight minutes, and the duration of action is one to two hours.

Concentration–Adverse Reaction Relationships

There is a relationship between increasing fentanyl plasma concentration and increasing frequency of dose-related opioid adverse reactions such as nausea, vomiting, CNS effects, and respiratory depression. In opioid-tolerant patients, the situation may be altered by the development of tolerance to opioid-related adverse reactions [see Dosage and Administration (2.1, 2.2)].

The onset of action of fentanyl is almost immediate when the drug is given intravenously; however, the maximal respiratory depressant effect may not be noted for several minutes. As with longer acting opioid analgesics, the duration of the respiratory depressant effect of fentanyl may be longer than the analgesic effect. The following observations have been reported concerning altered respiratory response to CO2 stimulation following administration of fentanyl citrate:

- Diminished sensitivity to CO2 stimulation may persist longer than depression of respiratory rate. (Altered sensitivity to CO2 stimulation has been demonstrated for up to four hours following a single dose of 600 mcg (0.6 mg) (12 mL) fentanyl citrate to healthy volunteers). Fentanyl frequently slows the respiratory rate, duration and degree of respiratory depression being dose-related.
- The peak respiratory depressant effect of a single intravenous dose of Fentanyl Citrate Injection is noted 5 to 15 minutes following injection [see Warnings and Precautions (5.2)].

12.3 Pharmacokinetics

Fentanyl Citrate Injection is administered by the intravenous or intramuscular route. The pharmacokinetics of fentanyl can be described as a three-compartment model.

Distribution

Fentanyl plasma protein binding decreases with increasing ionization of the drug. Alterations in pH may affect its distribution between plasma and the central nervous system. It accumulates in skeletal muscle and fat, and is released slowly into the blood. The volume of distribution for fentanyl is 4 L/kg. It has a distribution time of 1.7 minutes and redistribution time of 13 minutes.

Elimination

The terminal elimination half-life is 219 minutes.

Fentanyl, which is primarily transformed in the liver, demonstrates a high first-pass clearance and releases approximately 75% of an intravenous dose in urine, mostly as metabolites with less than 10% representing the unchanged drug. Approximately 9% of the dose is recovered in the feces, primarily as metabolites.

13 NONCLINICAL TOXICOLOGY

13.1 Carcinogenesis, Mutagenesis, Impairment of Fertility

Carcinogenesis

Long-term studies in animals to evaluate the carcinogenic potential of Fentanyl Citrate Injection have not been conducted.

Mutagenesis

Studies in animals to evaluate the mutagenic potential of Fentanyl Citrate Injection have not been conducted.

Impairment of Fertility

Decreased pregnancy rates occurred in a multigenerational study in which pregnant rats were treated subcutaneously during the first 21 days of pregnancy with 160 mcg/kg to 1250 mcg/kg fentanyl (0.26 times to 2.0 times a human dose of 100 mcg/kg based on body surface area).

Studies in animals to characterize the effect of fentanyl on male fertility have not been conducted.

16 HOW SUPPLIED/STORAGE AND HANDLING

Fentanyl Citrate Injection, USP equivalent to 50 mcg (0.05 mg) fentanyl per mL, is supplied in single-dose ampules and single-dose vials for intramuscular and intravenous administration, and available as follows:

Unit of Sale | Concentration
NDC 0409-9094-22 Tray containing 25, 2 mL Single-dose Fliptop Vials | 100 mcg Fentanyl/2 mL (50 mcg/mL)
NDC 0409-9094-25 Tray containing 25, 5 mL Single-dose Fliptop Vials | 250 mcg Fentanyl/5 mL (50 mcg/mL)
NDC 0409-9093-36 Carton containing 5, 10 mL Single-dose Ampules | 500 mcg Fentanyl/10 mL (50 mcg/mL)
NDC 0409-9094-28 Tray containing 25, 10 mL Single-dose Fliptop Vials | 500 mcg Fentanyl/10 mL (50 mcg/mL)
NDC 0409-9093-38 Carton containing 5, 20 mL Single-dose Ampules | 1000 mcg Fentanyl/20 mL (50 mcg/mL)
NDC 0409-9094-31 Tray containing 25, 20 mL Single-dose Fliptop Vials | 1000 mcg Fentanyl/20 mL (50 mcg/mL)
NDC 0409-9094-61 Tray containing 25, 50 mL Single-dose Fliptop Vials | 2500 mcg Fentanyl/50 mL (50 mcg/mL)

STORAGE AND HANDLING

Protect from light. Retain in carton until time of use.

Store at 20°C to 25°C (68°F to 77°F). [see USP Controlled Room Temperature.]

17 PATIENT COUNSELING INFORMATION

Addiction, Abuse, and Misuse ‎

Inform patients that the use of Fentanyl Citrate Injection, even when taken as recommended, can result in ‎addiction, abuse, and misuse, which can lead to overdose and death [see Warnings and Precautions (5.1)]. ‎

Life-Threatening Respiratory Depression

Inform patients of the risk of life-threatening respiratory depression, including information that the risk is ‎greatest when starting Fentanyl Citrate Injection or when the dosage is increased, and that it can occur ‎even at recommended dosages ‎[see Warnings and Precautions (5.2)]‎.‎

Hyperalgesia and Allodynia

Advise ‎patients to inform their healthcare provider if they ‎experience symptoms of hyperalgesia, including worsening ‎pain, increased ‎sensitivity to pain, or new pain [see Warnings and Precautions (5.7), ‎Adverse Reactions (6)].‎

Serotonin Syndrome

Inform patients that opioids could cause a rare but potentially life-threatening condition called serotonin syndrome resulting from concomitant administration of serotonergic drugs. Warn patients of the symptoms of serotonin syndrome and to seek medical attention right away if ‎symptoms develop after discharge from the hospital.‎ Instruct patients to inform their healthcare provider if they are taking, or plan to take serotonergic medications [see Warnings and Precautions (5.8), Drug Interactions (7)].

Constipation

Advise patients of the potential for severe constipation, including management instructions and when to seek medical attention [see Clinical Pharmacology (12.2)].

Distributed by Hospira, Inc., Lake Forest, IL 60045 USA

LAB-0843-8.0

PRINCIPAL DISPLAY PANEL - 10 mL Ampule Label

10 mL Single-dose
Rx only

Discard unused portion

Fentanyl Citrate
Injection, USP
500 mcg Fentanyl/10 mL
(50 mcg/mL)

CII

FOR INTRAVENOUS USE BY HOSPITAL
PERSONNEL SPECIFICALLY TRAINED IN
THE USE OF NARCOTIC
ANALGESICS.

PRINCIPAL DISPLAY PANEL - 10 mL Ampule Carton

10 mL

Single-dose
5 Ampuls

Discard unused portion

NDC 0409-9093-36

Fentanyl Citrate Injection, USP
500 mcg Fentanyl/10 mL
(50 mcg/mL)

CII

Hospira

Protect from light. Retain in carton until time of use.

Each mL contains fentanyl (as the citrate) 50 mcg (0.05 mg). May contain sodium hydroxide and/or hydrochloric acid
for pH adjustment. pH 4.7 (4.0 to 7.5). Sterile, nonpyrogenic.
Usual dose: See insert. Store at 20 to 25°C (68 to 77°F). [See USP Controlled Room Temperature.]

PRINCIPAL DISPLAY PANEL - 20 mL Ampule Label

20 mL Single-dose

Discard unused portion
Rx only

Fentanyl
Citrate
Injection, USP

1000 mcg Fentanyl/20 mL
(50 mcg/mL)

FOR INTRAVENOUS USE BY HOSPITAL
PERSONNEL SPECIFICALLY TRAINED IN
THE USE OF NARCOTIC ANALGESICS.

Distributed by Hospira, Inc., Lake Forest, IL 60045 USA

NDC 0409-9093-31

Each mL contains fentanyl (as
the citrate) 50 mcg (0.05 mg).
May contain NaOH and/or HCl
for pH adjustment. pH 4.7 (4.0
to 7.5). Protect from light.
Retain in carton until time of
use. Store at 20 to 25°C (68 to
77°F). [See USP Controlled
Room Temperature.]

CII

Hospira

RL-7316

LOT ##-###-AA

EXP DMMMYYYY

PRINCIPAL DISPLAY PANEL - 20 mL Ampule Carton

20 mL
Single-dose
5 Ampuls

NDC 0409-9093-38
Contains 5 of NDC 0409-9093-31

Discard unused portion

Rx only

Fentanyl Citrate
Injection, USP

1000 mcg Fentanyl/20 mL
(50 mcg/mL)

CII

Protect from light.
Retain in carton until time of use.
FOR INTRAVENOUS ADMINISTRATION BY
HOSPITAL PERSONNEL SPECIFICALLY TRAINED
IN THE USE OF NARCOTIC ANALGESICS.

Distributed by
Hospira, Inc., Lake Forest, IL 60045 USA

Hospira

PRINCIPAL DISPLAY PANEL - 2 mL Vial Label

2 mL Single-dose
NDC 0409-9094-12
Rx only

Intravenous or
Intramuscular Use

Fentanyl Citrate
Inj., USP
CII
100 mcg Fentanyl/2 mL
(50 mcg/mL)

Distributed by Hospira, Inc.
Lake Forest, IL 60045 USA

Hospira

PAA224401

PRINCIPAL DISPLAY PANEL - 2 mL Vial Tray Top

2 mL
Single-dose
25 Fliptop Vials
Discard unused portion.
NDC 0409-9094-22
Contains 25 of NDC 0409-9094-12

Fentanyl Citrate
Injection, USP
100 mcg Fentanyl/2 mL
(50 mcg/mL)
CII

Protect from light.
Retain in tray until time of use.
For Intravenous or Intramuscular use.
Rx only

CA-7136

Distributed by
Hospira, Inc., Lake Forest, IL 60045 USA

Hospira

PRINCIPAL DISPLAY PANEL - 2 mL Vial Tray

2 mL
Single-dose 25 Fliptop Vials
NDC 0409-9094-22
Discard unused portion.

Fentanyl Citrate Inj., USP
100 mcg Fentanyl/2 mL
(50 mcg/mL)
Rx only
CII

Retain in tray until time of use.
Protect from light.
For Intravenous or Intramuscular use.

Hospira

PRINCIPAL DISPLAY PANEL - 5 mL Vial Label

5 mL Single-dose Vial
Rx only
NDC 0409-9094-18

Fentanyl Citrate
Injection, USP
CII

250 mcg Fentanyl/5 mL
(50 mcg/mL)

For I.V. or I.M. use.
Protect from light.
Retain in tray until time of use.

Dist. by Hospira, Inc. Lake Forest, IL 60045 USA

PRINCIPAL DISPLAY PANEL - 5 mL Vial Tray Top

5 mL Single-dose
25 Fliptop Vials
Rx only
NDC 0409-9094-25
Contains 25 of NDC 0409-9094-18

Fentanyl Citrate
Injection, USP
CII

250 mcg Fentanyl/5 mL

(50 mcg/mL)

For Intravenous or Intramuscular use.
Protect from light.
Retain in tray until time of use.
Discard unused portion.

Distributed by
Hospira, Inc., Lake Forest, IL 60045 USA

Hospira

CA-7140

PRINCIPAL DISPLAY PANEL - 5 mL Vial Tray

5 mL Single-dose Vials
25 Units
NDC 0409-9094-25
Rx only

Fentanyl Citrate Injection, USP
CII
250 mcg Fentanyl/5 mL
(50 mcg/mL)

INTRAVENOUS or INTRAMUSCULAR USE. Protect from light.
Retain in tray until time of use. Discard unused portion.

Hospira

PRINCIPAL DISPLAY PANEL - 10 mL Vial Label

10 mL Single-dose Vial NDC 0409-9094-17

Discard unused portion. Rx only

Fentanyl Citrate Inj., USP
500 mcg Fentanyl/10 mL
CII
(50 mcg/mL)

Distributed by
Hospira, Inc., Lake Forest, IL 60045 USA

PRINCIPAL DISPLAY PANEL - 10 mL Vial Tray

10 mL Single-dose 25 Fliptop Vials
Discard unused portion
NDC 0409-9094-28
Contains 25 of NDC 0409-9094-17

Fentanyl Citrate Injection, USP CII

500 mcg Fentanyl/10 mL
(50 mcg/mL)
Rx only
Protect from light. Retain in carton until time of use.

Hospira

PRINCIPAL DISPLAY PANEL - 20 mL Vial Label

20 mL Single-dose Vial
NDC 0409-9094-16

Discard unused portion.
Rx only

Fentanyl Citrate
Injection, USP
CII

1000 mcg Fentanyl/20 mL
(50 mcg/mL)

Distributed by Hospira, Inc.,
Lake Forest, IL 60045 USA

Hospira

PRINCIPAL DISPLAY PANEL - 20 mL Vial Tray

20 mL Single-dose 25 Fliptop Vials
Discard unused portion.
Rx only
NDC 0409-9094-31
Contains 25 of NDC 0409-9094-16

Fentanyl Citrate Injection, USP
CII

1000 mcg Fentanyl/20 mL (50 mcg/mL)
Protect from light. Retain in carton until time of use.

Hospira

PRINCIPAL DISPLAY PANEL - 50 mL Vial Label

50 mL
Single-dose Vial
Discard unused portion.

Fentanyl Citrate
Injection, USP
2500 mcg Fentanyl/50 mL
CII

(50 mcg/mL)
Rx only

Distributed by Hospira, Inc.
Lake Forest, IL 60045 USA

Hospira

PRINCIPAL DISPLAY PANEL - 50 mL Vial Carton

One/NDC 0409-9094-41
Rx only

50 mL
Single-dose
Fliptop Vial

Discard unused portion.

Fentanyl
Citrate
Injection, USP
2500 mcg Fentanyl/50 mL
CII

(50 mcg/mL)

Protect from light.

Retain in carton
until time of use.

PRINCIPAL DISPLAY PANEL - 50 mL Vial Carton Tray

50 mL
Single-dose
25 Fliptop Vials
Discard unused portion.
NDC 0409-9094-61
Contains 25 of NDC 0409-9094-41
Rx only

Fentanyl Citrate Injection, USP
2500 mcg Fentanyl/50 mL
(50 mcg/mL)
CII

Protect from light. Retain in carton until time of use.

Hospira